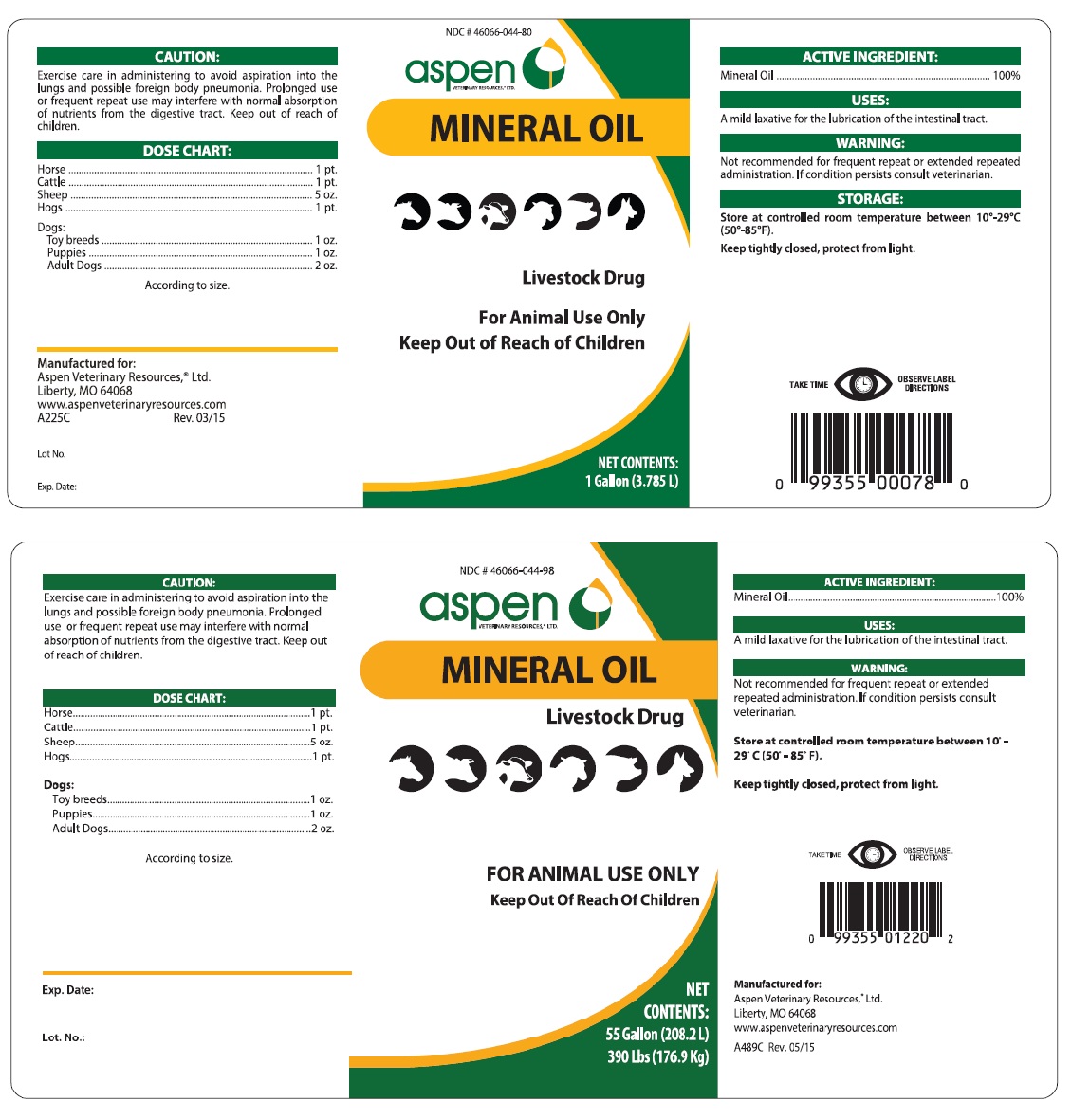 DRUG LABEL: Mineral Oil
NDC: 46066-044 | Form: OIL
Manufacturer: Aspen Veterinary
Category: animal | Type: OTC ANIMAL DRUG LABEL
Date: 20251126

ACTIVE INGREDIENTS: Light Mineral Oil 3.785 L/3.785 L

Mineral Oil

Mineral Oil

Livestock Drug

For animal use only

Keep out of reach of children

ACTIVE INGREDIENTS:

Mineral Oil................. 100%

USES: A mild laxative for the lubrication of the intestinal tract.

WARNING: Not recommended for frequent repeat or extended repeated administration. If condition persists consult veterinarian.

STORAGE: Store at controlled room temperature between 10°-29°C (50°-85°F).

Keep tightly closed, protect from light.

CAUTION: Exercise care in administering to avoid aspiration into the lungs and possible foreign body pneumonia. Prolonged use or frequent repeat use may interfere with normal absorption of nutrient from the digestive tract. Keep out of reach of children.

DOSE CHART:

Horse......................................1 pt.

Cattle.......................................1 pt.

Sheep.......................................5 oz.

Hogs.........................................1 pt.

Dogs:

Toy breeds............................1 oz.

Puppies.................................1 oz.

Adult Dogs.............................2 oz.

According to size.